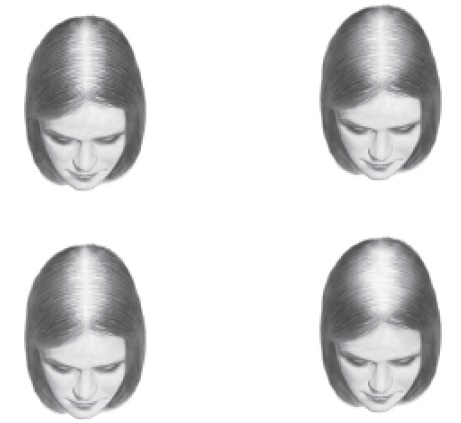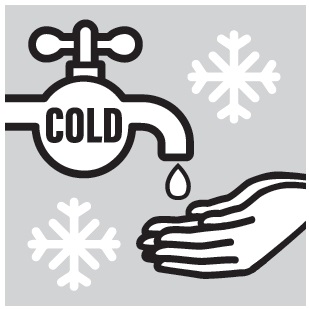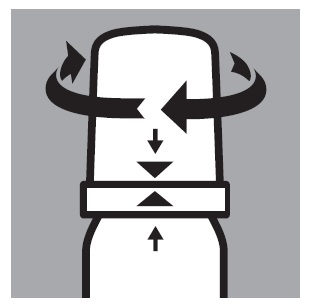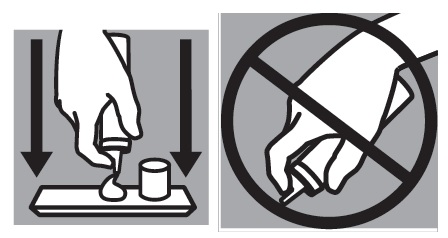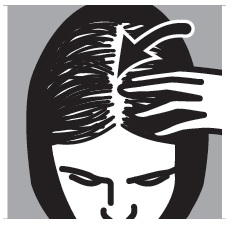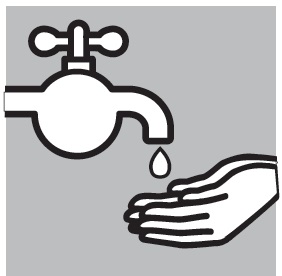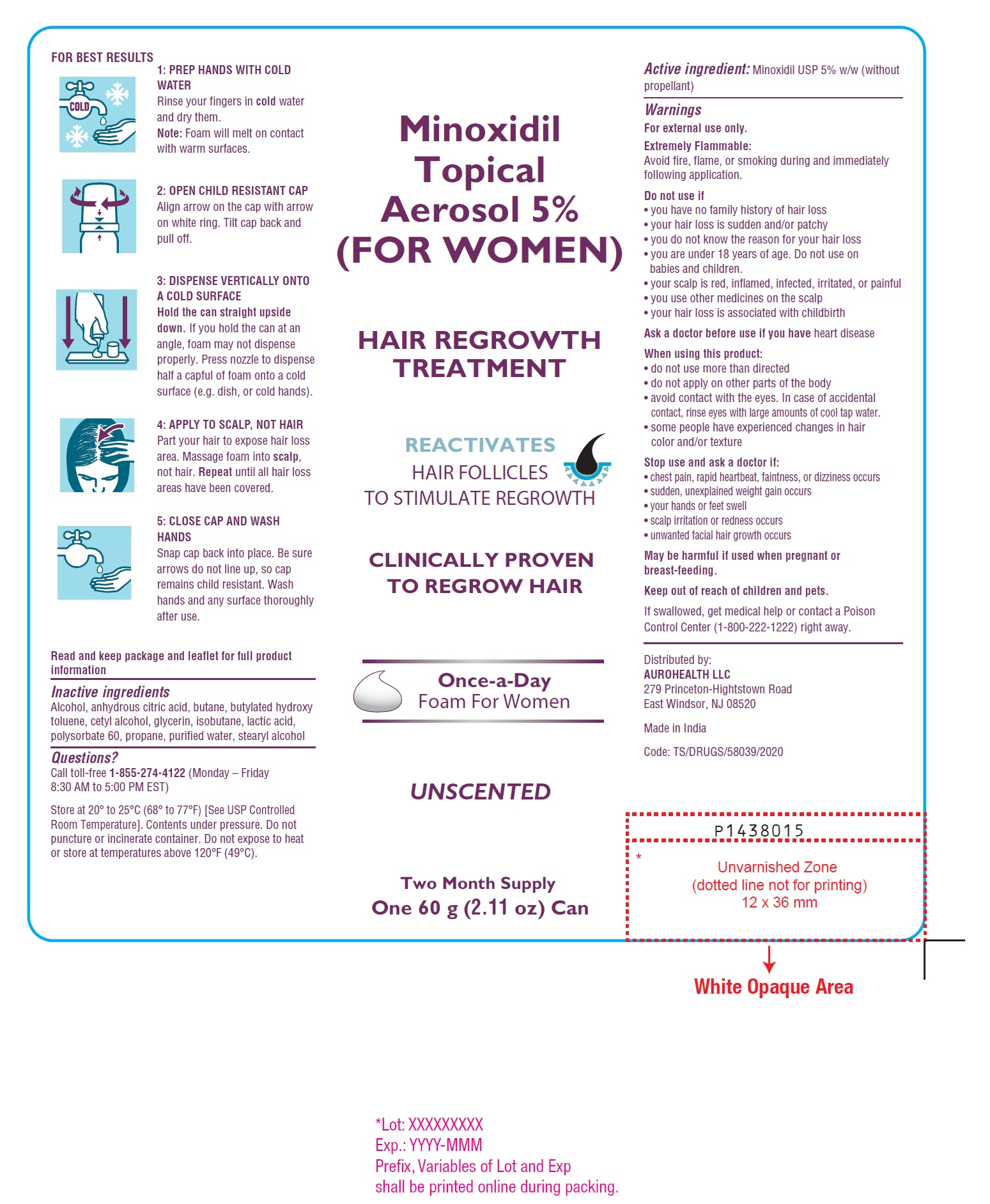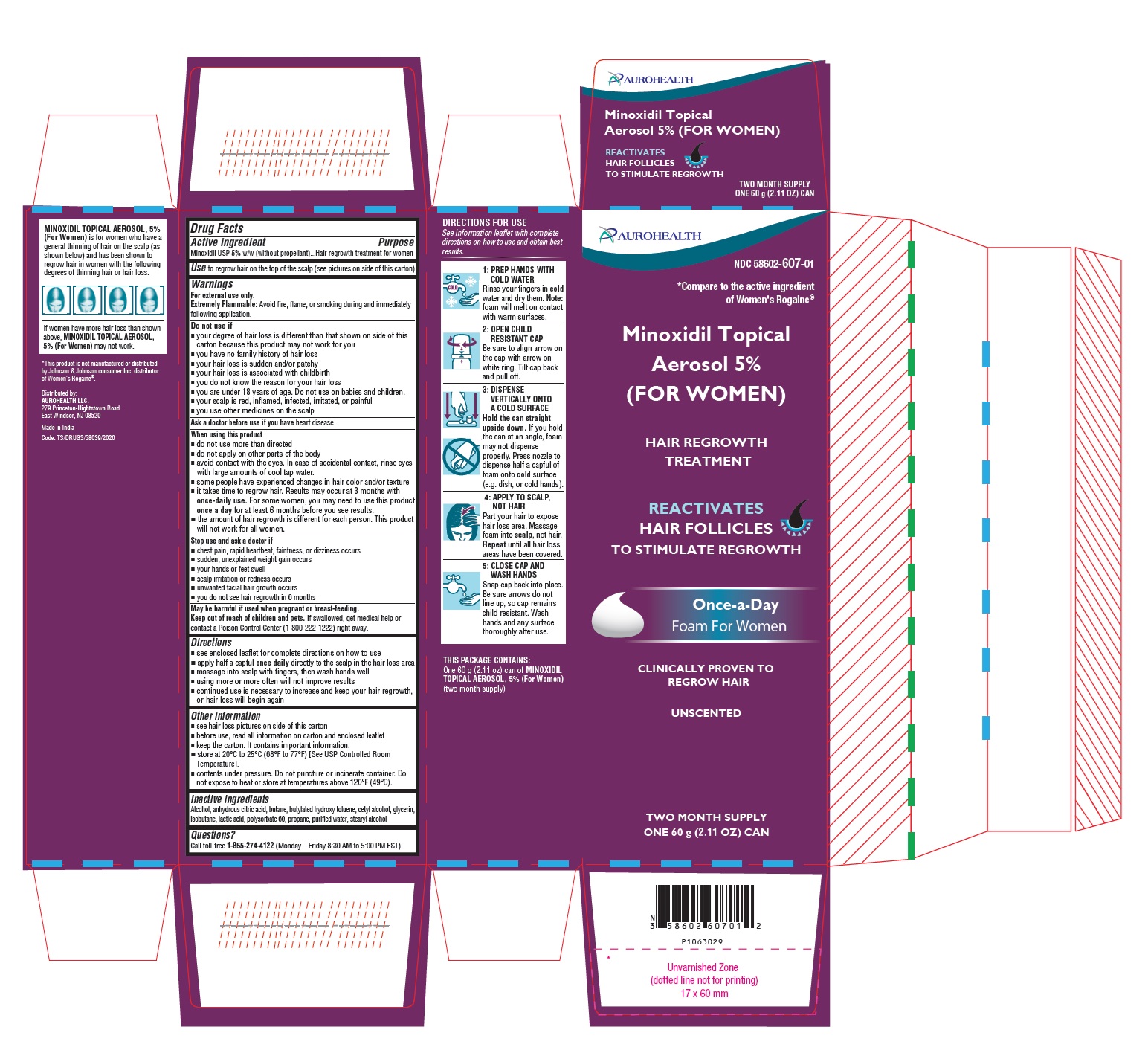 DRUG LABEL: MINOXIDIL 5% (FOR WOMEN)
NDC: 58602-607 | Form: AEROSOL, FOAM
Manufacturer: Aurohealth LLC
Category: otc | Type: Human OTC Drug Label
Date: 20260122

ACTIVE INGREDIENTS: MINOXIDIL 50 mg/1 g
INACTIVE INGREDIENTS: ALCOHOL; ANHYDROUS CITRIC ACID; BUTANE; BUTYLATED HYDROXYTOLUENE; CETYL ALCOHOL; GLYCERIN; ISOBUTANE; LACTIC ACID, UNSPECIFIED FORM; POLYSORBATE 60; PROPANE; WATER; STEARYL ALCOHOL

Active ingredient

Minoxidil USP 5% w/w (without propellant)

Purpose

Hair regrowth treatment for women

Use

to regrow hair on the top of the scalp (see pictures on side of this carton)

Warnings

For external use only.

Extremely Flammable: Avoid fire, flame, or smoking during and immediately following application.

Do not use if

- your degree of hair loss is different than that shown on side of this carton because this product may not work for you
- you have no family history of hair loss
- your hair loss is sudden and/or patchy
- your hair loss is associated with childbirth
- you do not know the reason for your hair loss
- you are under 18 years of age. Do not use on babies and children.
- your scalp is red, inflamed, infected, irritated, or painful
- you use other medicines on the scalp

Ask a doctor before use if you have heart disease

When using this product

- do not use more than directed
- do not apply on other parts of the body
- avoid contact with the eyes. In case of accidental contact, rinse eyes with large amounts of cool tap water.
- some people have experienced changes in hair color and/or texture
- it takes time to regrow hair. Results may occur at 3 months with once-daily use. For some women, you may need to use this product once a day for at least 6 months before you see results.
- the amount of hair regrowth is different for each person. This product will not work for all women.

Stop use and ask a doctor if

- chest pain, rapid heartbeat, faintness, or dizziness occurs
- sudden, unexplained weight gain occurs
- your hands or feet swell
- scalp irritation or redness occurs
- unwanted facial hair growth occurs
- you do not see hair regrowth in 6 months

PREGNANCY OR BREAST FEEDING

May be harmful if used when pregnant or breast-feeding.

Keep out of reach of children and pets. If swallowed, get medical help or contact a Poison Control Center (1-800-222-1222) right away.

Directions

- see enclosed leaflet for complete directions on how to use
- apply half a capful once daily directly to the scalp in the hair loss area
- massage into scalp with fingers, then wash hands well
- using more or more often will not improve results
- continued use is necessary to increase and keep your hair regrowth, or hair loss will begin again

Other information

- see hair loss pictures on side of this carton
- before use, read all information on carton and enclosed leaflet
- keep the carton. It contains important information.
- store at 20°C to 25°C (68°F to 77°F) [See USP Controlled Room Temperature].
- contents under pressure. Do not puncture or incinerate container. Do not expose to heat or store at temperatures above 120°F (49°C).

Inactive ingredients

Alcohol, anhydrous citric acid, butane, butylated hydroxy toluene, cetyl alcohol, glycerin, isobutane, lactic acid, polysorbate 60, propane, purified water, stearyl alcohol

Questions?

Call toll-free 1-855-274-4122 (Monday – Friday 8:30 AM to 5:00 PM EST)

Distributed by:
AUROHEALTH LLC.
279 Princeton-Hightstown Road
East Windsor, NJ 08520
Made in India

Code: TS/DRUGS/58039/2020

IMPORTANT INFORMATION ABOUT

Minoxidil Topical Aerosol 5% (For Women)

Hair Regrowth Treatment

REACTIVATES HAIR FOLLICLES TO STIMULATE REGROWTH

CLINICALLY PROVEN TO REGROW HAIR

Once–a-Day

Foam For Women

UNSCENTED

Minoxidil Topical Aerosol 5% (For Women)

Hair Regrowth Treatment

Save this leaflet for future reference.

Please read this leaflet carefully. It will help you understand how to use Women’s Minoxidil Topical Aerosol 5% (Foam) and what to expect from its use. It takes time to regrow hair. Results may occur at 3 months with once daily usage. For some women, you may need to use this product for at least 6 months before you see results. If you have any questions after reading this leaflet, or anytime while using Women’s Minoxidil Topical Aerosol 5% (Foam), you should ask your health care professional or call us at toll-free 1-855-274-4122 (Monday – Friday 8:30 AM to 5:00 PM EST).

WHAT IS WOMEN’S MINOXIDIL TOPICAL AEROSOL 5% (FOAM)?

Women’s Minoxidil Topical Aerosol 5% (Foam) is a white foam containing 5% minoxidil for use only on the scalp to help regrow hair in women.

WHO MAY USE WOMEN’S MINOXIDIL TOPICAL AEROSOL 5% (FOAM)?

Women’s Minoxidil Topical Aerosol 5% (Foam) may be appropriate for you if you are an adult who is at least 18 years old and experiencing gradually thinning hair or gradual hair loss on the top of your scalp. The common hereditary thinning or hair loss process begins slowly and may become noticeable only after years of gradual loss.

Women’s Minoxidil Topical Aerosol 5% (Foam) is for general thinning of hair on the top of the scalp as shown below. Women’s Minoxidil Topical Aerosol 5% (Foam) has been shown to regrow hair in women with the degrees of hair loss shown. If women have more hair loss than shown, Women’s Minoxidil Topical Aerosol 5% (Foam) may not work.

Many of those experiencing hair loss have other family members with gradual thinning hair or hair loss. If there is no family history of gradual thinning or gradual hair loss, or hair loss is patchy, see your doctor.

WHO SHOULD NOT USE WOMEN’S MINOXIDIL TOPICAL AEROSOL 5% (FOAM)?

Women’s Minoxidil Topical Aerosol 5% (Foam) will not prevent or improve hair loss related to pregnancy, the use of some prescription and non-prescription medications, certain severe nutritional problems (very low body iron; excessive vitamin A intake), the recently discontinued use of birth control pills, low thyroid states (hypothyroidism), chemotherapy, or diseases which cause scarring of the scalp. Also, Women’s Minoxidil Topical Aerosol 5% (Foam) will not improve hair loss due to:

- Damage from the use of hair care products which cause scarring or deep burns of the scalp.
- Hair grooming methods such as cornrowing or ponytails which require pulling the hair tightly back from the scalp.

Do not use if you are not sure of the reason for your hair loss.

WILL WOMEN’S MINOXIDIL TOPICAL AEROSOL 5% (FOAM) WORK FOR ME?

The amount of hair regrowth is different for each person. Not everyone will respond to Women’s Minoxidil Topical Aerosol 5% (Foam). The response to Women’s Minoxidil Topical Aerosol 5% (Foam) cannot be predicted. No one will be able to grow back all their hair.
To see your best results with Women’s Minoxidil Topical Aerosol 5% (Foam), make sure you apply the product directly to the scalp once daily. For some women, Women’s Minoxidil Topical Aerosol 5% (Foam) may not work.

HOW SOON CAN I EXPECT RESULTS FROM USING WOMEN’S MINOXIDIL TOPICAL AEROSOL 5% (FOAM)?

Since normal hair usually grows only 1/2 to 1 inch per month, hair regrowth with Women’s Minoxidil Topical Aerosol 5% (Foam) also takes time. Generally, new hair growth is slow for a Women’s Minoxidil Topical Aerosol 5% (Foam) user. Results may be seen as early as 3 months with once daily use. For some women, it may take at least 6 months for results to be seen. If you do not see any results after 6 months, stop using Women’s Minoxidil Topical Aerosol 5% (Foam) and seek the advice of your doctor.

When you first begin to use Women’s Minoxidil Topical Aerosol 5% (Foam), your hair loss may continue for up to 2 weeks. This increase in hair loss is expected and is temporary. However, if it continues after two weeks, see your physician.

IF WOMEN’S MINOXIDIL TOPICAL AEROSOL 5% (FOAM) IS WORKING, WHAT WILL THE HAIR LOOK LIKE?

At first, hair growth may be soft, downy, and colorless hairs. After further use, the new hairs should be the same color and thickness as the other hairs on your scalp.

HOW LONG DO I NEED TO USE WOMEN’S MINOXIDIL TOPICAL AEROSOL 5% (FOAM)?

If you respond to Women’s Minoxidil Topical Aerosol 5% (Foam), you need to use it once daily to keep and continue the hair regrowth. Up to 3 months of usage may be needed to see your best results from Women’s Minoxidil Topical Aerosol 5% (Foam).

WHAT HAPPENS IF I COMPLETELY STOP USING WOMEN’S MINOXIDIL TOPICAL AEROSOL 5% (FOAM)? WILL I KEEP THE NEW HAIR?

Continuous use of Women’s Minoxidil Topical Aerosol 5% (Foam) is needed to maintain hair regrowth. If you stop using Women’s Minoxidil Topical Aerosol 5% (Foam), the normal hair loss process will start again. You will probably lose your newly regrown hair in three to four months.

HOW DO I USE WOMEN’S MINOXIDIL TOPICAL AEROSOL 5% (FOAM)?

For best results, apply half a capful once a day directly to the scalp in the hair loss area. Using more than the recommended amount will not improve results. Each can should last two months, if used as directed. Never take this product by mouth or apply to other parts of the body. Please refer to the “Directions for Use” section of this leaflet.
WHEN DO I USE WOMEN’S MINOXIDIL TOPICAL AEROSOL 5% (FOAM)?

Apply Women’s Minoxidil Topical Aerosol 5% (Foam) once daily. If you apply at night, allow application to dry completely before going to bed.

WHAT IF I FORGET TO USE WOMEN’S MINOXIDIL TOPICAL AEROSOL 5% (FOAM) OR MISS A DOSE?

If you miss one daily dose of Women’s Minoxidil Topical Aerosol 5% (Foam), just continue with your next dose. You should not make up for missed doses.

CAN I USE WOMEN’S MINOXIDIL TOPICAL AEROSOL 5% (FOAM) MORE THAN ONCE A DAY? WILL IT WORK FASTER, BETTER?

No. Women’s Minoxidil Topical Aerosol 5% (Foam) will not work faster or better if used more than once a day. More frequent use or larger doses have not been shown to speed up hair growth and may increase your chances of side effects.

WHAT KIND OF SHAMPOO SHOULD I USE WITH WOMEN’S MINOXIDIL TOPICAL AEROSOL 5% (FOAM)?

If you wash your scalp before applying Women’s Minoxidil Topical Aerosol 5% (Foam), use a mild shampoo.

CAN I USE HAIR SPRAYS, MOUSSES, CONDITIONERS, GELS, ETC.?

Yes. There is no reason to change your usual hair care routine when using Women’s Minoxidil Topical Aerosol 5% (Foam). However, you should apply Women’s Minoxidil Topical Aerosol 5% (Foam) first and wait for it to dry before applying your styling aids.

CAN I HAVE MY HAIR COLORED OR PERMED OR USE HAIR RELAXERS WHILE USING WOMEN’S MINOXIDIL TOPICAL AEROSOL 5% (FOAM)?

Yes. We have no evidence that coloring, perming, or using relaxers on your hair change the effect of Women’s Minoxidil Topical Aerosol 5% (Foam). However, because the use of a permanent wave and hair color can cause scalp irritation on certain people, we recommend the following precautions:

1. To avoid possible scalp irritation, you should make sure all of the Women’s Minoxidil Topical Aerosol 5% (Foam) has been washed off the hair and scalp before using color or perm chemicals.
2. For best results, do not apply Women’s Minoxidil Topical Aerosol 5% (Foam) on the same day that you use a chemical treatment on your hair.
3. Do not use Women’s Minoxidil Topical Aerosol 5% (Foam) for 24 hours after using any chemicals to make sure your scalp has not been irritated by the perm or color treatment. If no irritation occurs, continue use of Women’s Minoxidil Topical Aerosol 5% (Foam) as usual.
4. Simply restart your normal Women’s Minoxidil Topical Aerosol 5% (Foam) routine. There is no need to use more Women’s Minoxidil Topical Aerosol 5% (Foam) to make up for missed applications.

Missing one day of Women’s Minoxidil Topical Aerosol 5% (Foam) will not affect your hair regrowth results.

CAN I APPLY WOMEN’S MINOXIDIL TOPICAL AEROSOL 5% (FOAM) AND WASH MY HAIR AN HOUR LATER?

No. For Women’s Minoxidil Topical Aerosol 5% (Foam) to work best, you should allow Women’s Minoxidil Topical Aerosol 5% (Foam) to remain on the scalp for about 4 hours before washing.

DIRECTIONS FOR USE:

- Please familiarize yourself with the instructions below in order to help make your product application a success.
- This product should be used ONCE DAILY, EVERY DAY.
- To be effective, it is important to apply the product DIRECTLY TO YOUR SCALP and NOT TO YOUR HAIR so that it can easily get to your hair follicles to help regrow your hair.
- There is no need to shampoo your hair before using the product. If you wish to shampoo your hair before applying Women’s Minoxidil Topical Aerosol 5% (Foam), towel dry your hair so that the skin on the scalp is dry.

1: PREP HANDS WITH COLD WATER

Rinse your fingers in cold water and dry them. Note: foam will melt on contact with warm surfaces.
2: OPEN CHILD RESISTANT CAP

Be sure to align arrow on the cap with arrow on white ring. Tilt cap back and pull off.
3: DISPENSE VERTICALLY ONTO A COLD SURFACE

Hold the can straight upside down.

If you hold the can at an angle, foam may not dispense properly. Press nozzle to dispense half a capful of foam onto a cold, surface (e.g. dish, or cold hands).

4: APPLY TO SCALP, NOT HAIR

Part your hair to expose hair loss area. Massage foam into scalp, not hair. Repeat until all hair loss areas have been covered.

5: CLOSE CAP AND WASH HANDS
Snap cap back into place. Be sure arrows do not line up, so cap remains child resistant. Wash hands and any surface thoroughly after use.

ARE THERE ANY SPECIAL WARNINGS ABOUT THE USE OF WOMEN’S MINOXIDIL TOPICAL AEROSOL 5% (FOAM)?

Warnings:

For external use only.

Extremely Flammable: Avoid fire, flame, or smoking during and immediately following application.

DO NOT USE IF

- your degree of hair loss is more than that shown on the other side of this leaflet, because this product may not work for you
- you have no family history of hair loss
- your hair loss is sudden and/or patchy
- your hair loss is associated with childbirth
- you do not know the reason for your hair loss
- you are under 18 years of age. Do not use on babies and children.
- your scalp is red, inflamed, infected, irritated, or painful
- you use other medicines on the scalp

Ask a doctor before use if you have heart disease.

WHEN USING THIS PRODUCT

- do not use more than directed
- do not apply on other parts of the body
- avoid contact with the eyes. In case of accidental contact, rinse eyes with large amounts of cool tap water.
- contact between children and minoxidil application sites should be avoided. Cases of excessive hair growth have been reported in infants following skin contact with minoxidil application sites of caregivers using topical minoxidil. Excessive hair growth was reversible, within months, when infants were no longer exposed to minoxidil.
- some people have experienced changes in hair color and/or texture
- it takes time to regrow hair. Results may occur in 3 months with once daily use. For some women you may need to use this product once daily for at least 6 months before you see results.
- the amount of hair regrowth is different for each person. This product will not work for everyone.

STOP USE AND ASK A DOCTOR IF

- chest pain, rapid heartbeat, faintness, or dizziness occurs
- sudden, unexplained weight gain occurs
- your hands or feet swell
- scalp irritation or redness occurs
- unwanted facial hair growth occurs
- you do not see hair regrowth in 6 months

May be harmful if used when pregnant or breast-feeding.

Keep out of reach of children and pets.

If swallowed, get medical help or contact a poison control center (1-800-222-1222) right away.

WHAT ARE THE MOST COMMON SIDE EFFECTS WITH WOMEN’S MINOXIDIL TOPICAL AEROSOL 5% (FOAM)?

The most common side effects are itching and other skin irritations of the treated area of the scalp. Women’s Minoxidil Topical Aerosol 5% (Foam) contains alcohol, which would cause burning or irritation of the eyes or sensitive skin areas. If Women’s Minoxidil Topical Aerosol 5% (Foam) accidentally gets into these areas, rinse with large amounts of cool tap water. Stop using Women’s Minoxidil Topical Aerosol 5% (Foam) and contact your doctor if irritation persists.
CAN WOMEN’S MINOXIDIL TOPICAL AEROSOL 5% (FOAM) PRODUCE UNWANTED HAIR?

Unwanted hair growth has been reported on the face and on other parts of the body with Women’s Minoxidil Topical Aerosol 5% (Foam) use. The unwanted hair growth may be caused by the transfer of Women’s Minoxidil Topical Aerosol 5% (Foam) to areas other than the scalp, or by absorption into the circulatory system of low levels of the active ingredient, or by a medical condition not related to the use of Women’s Minoxidil Topical Aerosol 5% (Foam).

If you experience unwanted hair, discontinue using Women’s Minoxidil Topical Aerosol 5% (Foam) and see your doctor for recommendations about appropriate treatment. After stopping use of Women’s Minoxidil Topical Aerosol 5% (Foam), the unwanted hair, if caused by the use of Women’s Minoxidil Topical Aerosol 5% (Foam), should go away over time. You can take steps to decrease the chances for unwanted hair growth:

1. Limit the application of Women’s Minoxidil Topical Aerosol 5% (Foam) only to the scalp,
2. If you use the hands to apply Women’s Minoxidil Topical Aerosol 5% (Foam), wash your hands thoroughly afterwards, and
3. Allow sufficient drying time before going to bed (usually 2 to 4 hours before going to bed after applying Women’s Minoxidil Topical Aerosol 5% (Foam).

CAN I USE WOMEN’S MINOXIDIL TOPICAL AEROSOL 5% (FOAM) FOR BALDNESS OR HAIR LOSS IN BABIES AND CHILDREN?

No. Women’s Minoxidil Topical Aerosol 5% (Foam) must not be used to treat baldness or hair loss in babies or children.

WHAT FACTORS MAY INCREASE THE RISK OF SERIOUS SIDE EFFECTS WITH WOMEN’S MINOXIDIL TOPICAL AEROSOL 5% (FOAM)?

Women’s Minoxidil Topical Aerosol 5% (Foam) should be applied only to the scalp. The risk of side effects may be greater when Women’s Minoxidil Topical Aerosol 5% (Foam) is applied to other parts of the body.

If you have any other questions, ask your health care professional or call us toll-free 1-855-274-4122 (Monday – Friday 8:30 AM to 5:00 PM EST).

Store at 20°C to 25°C (68°F to 77°F) [See USP Controlled Room Temperature]. Contents under pressure. Do not puncture or incinerate container. Do not expose to heat or store at temperatures above 120°F (49°C).

Save this leaflet for future reference.
Distributed by:
AUROHEALTH LLC
279 Princeton-Hightstown Road
East Windsor, NJ 08520
Questions? Call toll-free 1-855-274-4122 (Monday – Friday 8:30 AM to 5:00 PM EST)
Revised: 01/2026

PRINCIPAL DISPLAY PANEL - One 60 g Can Label

Minoxidil
Topical
Aerosol 5%
(FOR WOMEN)
HAIR REGROWTH
TREATMENT
REACTIVATES
HAIR FOLLICLES
TO STIMULATE REGROWTH
CLINICALLY PROVEN
TO REGROW HAIR
Once-a-Day
Foam For Women

UNSCENTED

Two Month Supply
One 60 g (2.11 oz) Can

PRINCIPAL DISPLAY PANEL - One 60 g Can Carton

AUROHEALTH

NDC 58602-607-01

*Compare to the active ingredient
of Women's Rogaine®

Minoxidil Topical
Aerosol 5%
(FOR WOMEN)
HAIR REGROWTH
TREATMENT
REACTIVATES
HAIR FOLLICLES
TO STIMULATE REGROWTH
Once-a-Day
Foam For Women
CLINICALLY PROVEN TO
REGROW HAIR

UNSCENTED

TWO MONTH SUPPLY
ONE 60 g (2.11 oz) CAN